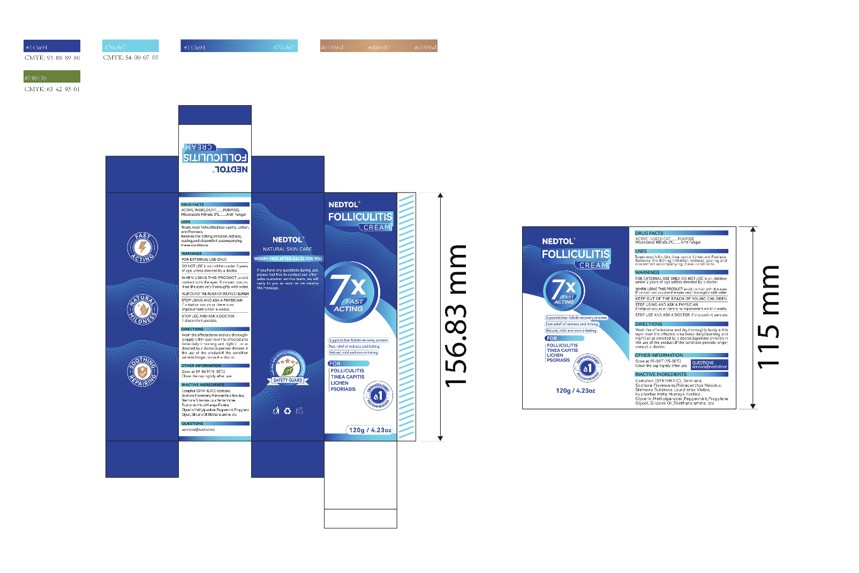 DRUG LABEL: Nedtol Folliculitis Treatment Creams
NDC: 84867-022 | Form: CREAM
Manufacturer: Jiashen International Trade Limited
Category: otc | Type: HUMAN OTC DRUG LABEL
Date: 20250823

ACTIVE INGREDIENTS: MICONAZOLE NITRATE 2 g/100 g
INACTIVE INGREDIENTS: RHINACANTHUS NASUTUS WHOLE; VIOLA PATRINII; PROPYLENE GLYCOL; WATER; GENTIANELLA AMARELLA ROOT; MURRAYA PANICULATA LEAFY TWIG; TROLAMINE; DIMETHICONE; SOPHORA FLAVESCENS ROOT; STEMONA TUBEROSA WHOLE; GLYCERIN; CAMPHOR (SYNTHETIC); EUPHORBIA HIRTA; PEPPERMINT; METHYLPARABEN

ACTIVE INGREDIENT

Miconazole Nitrate 2%.Anti-fungal

WARNINGS

FOR EXTERNAL USE ONLY.

DO NOT USE it on children under 2 yearsof age unless directed by a doctor.WHEN USING THIS PRODUCT,avoidcontact with the eyes, lf contact occurs,rinse the eyes very thoroughly with water.KEEP OUT OF THE REACH OF YOUING CHILDRENSTOP USING AND ASK A PHYSICIANif irritation occurs or there is noirmmprovement within 4 weeks,STOP USE AND ASK A DOCTORif discomfort persists.

KEEP OUT OF THE REACH OF YOUING CHILDREN

STOP USE

STOP USING AND ASK A PHYSICIANif irritation oocurs or there is no improwement within 4 weeks

PURPOSE

FOLLICULITISTINEA CAPITISLICHENPSORIASIS

INDICATIONS AND USAGE

Treats most folliculitis,tinea capitis, Lichen,.and Psoriasis.Relieves the itching,irritation,redness,scaling,and discomfort accompanyingthese conditions.

DOSAGE AND ADMINISTRATION

Wash the affectedarea and dry thorough-ly.Apply a thin layer over the affected areatwice daily (morning and night), or asdirected by a doctor,Supervise children inthe use of the product.lf the conditionpersists longer, consult a doctor.

OTHER INFORMATION
Store at 59-86F(15-30°C)Close the cap tightly after use.

INACTIVE INGREDIENT

Water
Camphor(SYNTHETIC)
Gentiana
Sophora Flavescens
Rhinacanthus Nasutus
Stemona Tuberosa Lour
Herba Violae
Euphorbia Hirta
Murraya Exotica
Peppermint
Glycerin
Methylparaben
Propylene Glycol
Silicone Oil
Triethanolamine